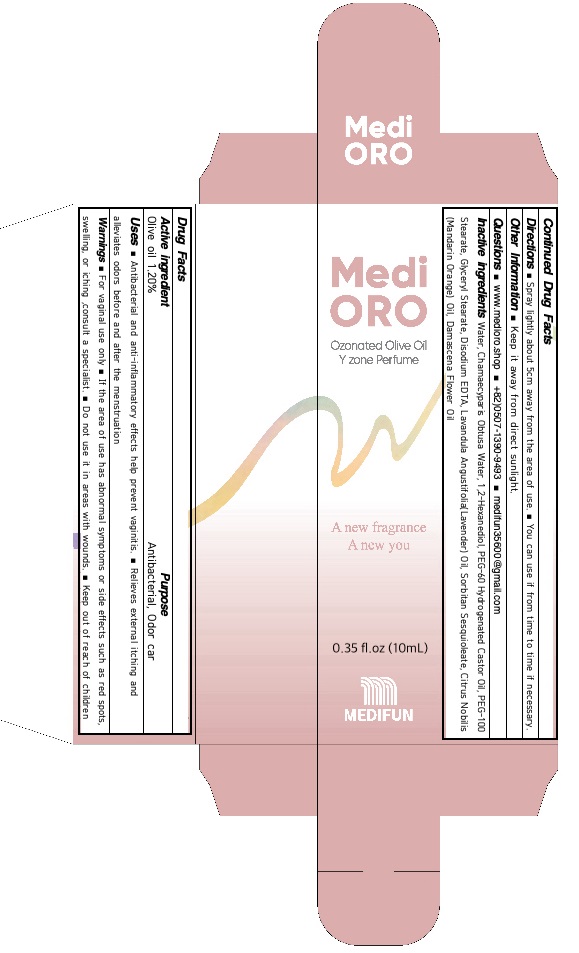 DRUG LABEL: MediORO W
NDC: 82363-010 | Form: SPRAY
Manufacturer: MEDIFUN Inc.
Category: otc | Type: HUMAN OTC DRUG LABEL
Date: 20211103

ACTIVE INGREDIENTS: OLIVE OIL 0.12 g/10 mL
INACTIVE INGREDIENTS: Water; CHAMAECYPARIS OBTUSA WOOD OIL; 1,2-Hexanediol

ACTIVE INGREDIENT

Olive oil 1.20%

PURPOSE

Antibacterial, Odor care

Uses

■ Antibacterial and anti-inflammatory effects help prevent vaginitis.
■ Relieves external itching and alleviates odors before and after the menstruation

WARNINGS

For vaginal use only
If the area of use has abnormal symptoms or side effects such as red spots, swelling, or iching, consult a specialist.
Do not use it in areas with wounds.
Don’t use it right after removing the fur.
Keep out of reach of children

KEEP OUT OF REACH OF CHILDREN

Directions

■ Spray lightly about 5cm away from the area of use.
■ You can use if from time to time if necessary.

Other Information

■ Do not store this product in an inappropriate place such as high or low temperatures or under direct sun light

Questions

■ www.medioro.shop / +82) 0507-1390-9493 / medifun35600@gmail.com

INACTIVE INGREDIENTS

Water, Chamaecyparis Obtusa Water, 1,2-Hexanediol, PEG-60 Hydrogenated Castor Oil, PEG-100 Stearate, Glyceryl Stearate, Disodium EDTA, Lavandula Angustifolia (Lavender) Oil, Sorbitan Sesquioleate, Citrus Nobilis (Mandarin Orange) Oil, Damascena Flower Oil